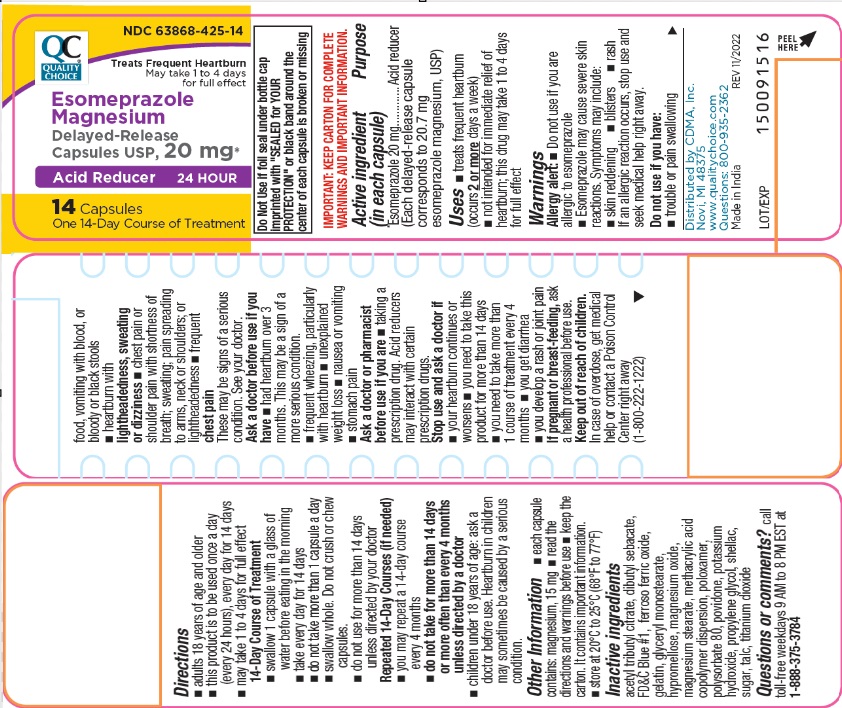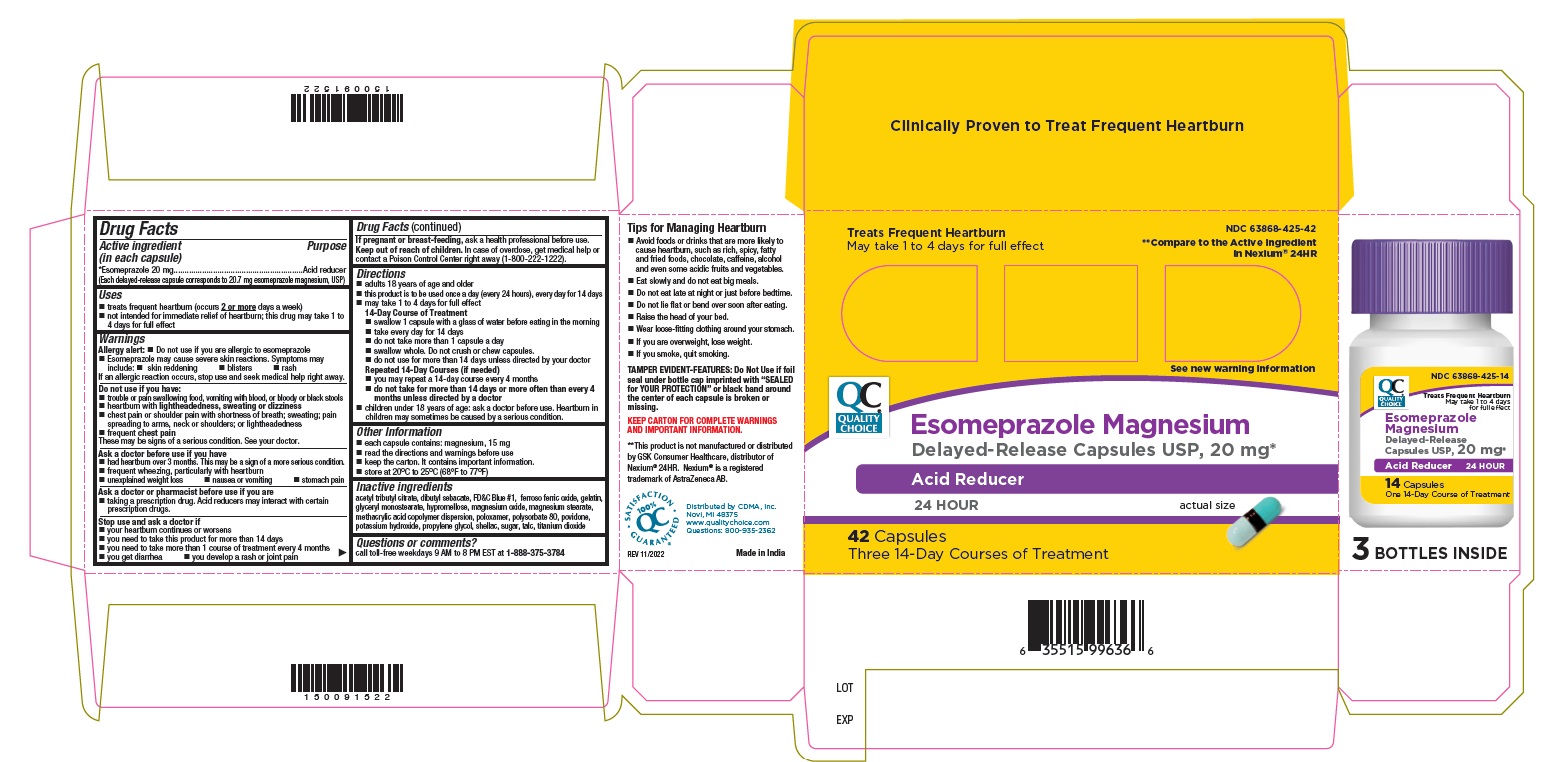 DRUG LABEL: Esomeprazole Magnesium
NDC: 63868-425 | Form: CAPSULE, DELAYED RELEASE
Manufacturer: CHAIN DRUG MARKETING ASSOCIATION INC
Category: otc | Type: HUMAN OTC DRUG LABEL
Date: 20251028

ACTIVE INGREDIENTS: Esomeprazole Magnesium 20 mg/1 1
INACTIVE INGREDIENTS: acetyltributyl citrate; Dibutyl Sebacate; Ferrosoferric Oxide; Gelatin; Glyceryl Monostearate; Hypromelloses; Magnesium Oxide; Magnesium Stearate; Methacrylic Acid - Ethyl Acrylate Copolymer (1:1) Type A; Poloxamer 188; Polysorbate 80; Povidone K30; Talc; Titanium Dioxide; PROPYLENE GLYCOL; Potassium Hydroxide; Shellac; Sucrose; Fd&C Blue No. 1

Drug Facts

Active ingredient (in each capsule)

*Esomeprazole 20 mg

(Each delayed-release capsule corresponds to 20.7 mg esomeprazole magnesium, USP)

Purpose

Acid reducer

Use(s)

- treats frequent heartburn (occurs 2 or more days a week)
- not intended for immediate relief of heartburn; this drug may take 1 to 4 days for full effect

Warnings

Allergy alert: Do not use if you are allergic to esomeprazole

- Esomeprazole may cause severe skin reactions. Symptoms may include:
- skin reddening
- blisters
- rash

If an allergic reaction occurs, stop use and seek medical help right away

Do not use if you have:

- trouble or pain swallowing food, vomiting with blood, or bloody or black stools
- heartburn with lightheadedness, sweating or dizziness
- chest pain or shoulder pain with shortness of breath; sweating; pain spreading to arms, neck or shoulders; or lightheadness
- frequent chest pain.

These may be signs of a serious condition. See your doctor.

Ask a doctor before use if you have

- had heartburn over 3 months. This may be a sign of a more serious condition.
- frequent wheezing, particularly with heartburn
- unexplained weight loss
- nausea or vomiting
- stomach pain

Ask a doctor or pharmacist before use if you are

- taking a prescription drug. Acid reducers may interact with certain prescription drugs.

Stop use and ask doctor if

- your heartburn continues or worsens
- you need to take this product for more than 14 days
- you need to take more than 1 course of treatment every 4 months
- you get diarrhea
- you develop a rash or joint pain

If pregnant or breast-feeding, ask a health professional before use.

Keep out of reach of children.

In case of overdose, get medical help or contact a Poison Control Center right away (1-800-222-1222).

Directions

- adults 18 years of age and older
- this product is to be used once a day (every 24 hours), every day for 14 days
- may take 1 to 4 days for full effect

14-Day Course of Treatment

- swallow 1 capsule with a glass of water before eating in the morning
- take every day for 14 days
- do not take more than 1 capsule a day
- swallow whole. Do not crush or chew capsules
- do not use for more than 14 days unless directed by your doctor

Repeated 14-Day Courses (if needed)

- you may repeat a 14-day course every 4 months
- do not take for more than 14 days or more often than every 4 months unless directed by a doctor

- children under 18 years of age: ask a doctor before use. Heartburn in children may sometimes be caused by a serious condition.

Other information

- each capsule contains: magnesium, 15 mg
- read directions and warnings before use
- keep the carton. It contains important information
- store at 20 to 25°C (68 to 77°F)

Inactive ingredients

acetyl tributyl citrate, dibutyl sebacate, FD&C Blue #1, ferroso ferric oxide, gelatin, glyceryl monostearate, hypromellose, magnesium oxide, magnesium stearate, methacrylic acid copolymer dispersion, poloxamer, polysorbate 80, povidone, potassium hydroxide, propylene glycol, shellac, sugar, talc, titanium dioxide

Questions or comments?

call toll-free weekdays 9 AM to 8 PM EST at 1-888-375-3784

Tips for Managing Heartbun

- Avoid foods or drinks that are more likely to cause heartburn, such as rich, spicy, fatty and fried foods, chocolate, caffeine, alcohol and even some acidic fruits and vegetables.
- Eat slowly and do not eat big meals.
- Do not eat late at night or just before bedtime.
- Do not lie flat or bend over soon after eating.
- Raise the head of your bed.
- Wear loose-fitting clothing around your stomach.
- If you are overweight, lose weight.
- If you smoke, quit smoking.

Bottle Label

NDC 63868-425-14

QC QUALITY CHOICE

Treats Frequent Heartburn
May take 1 to 4 days
for full effect

Esomeprazole
Magnesium
Delayed-Release
Capsules USP, 20 mg*
Acid Reducer 24 HOUR

14 Capsules
One 14-Day Course of Treatment

Carton Label

NDC 63868-425-42

QC QUALITY CHOICE

**Compare to the
Active Ingredient in
Nexium® 24HR

Treats Frequent Heartburn
May take 1 to 4 days
for full effect

Esomeprazole
Magnesium

Delayed-Release
Capsules USP, 20 mg*
Acid Reducer

24 HOUR

42 Capsules
Three 14-Day Courses of Treatment